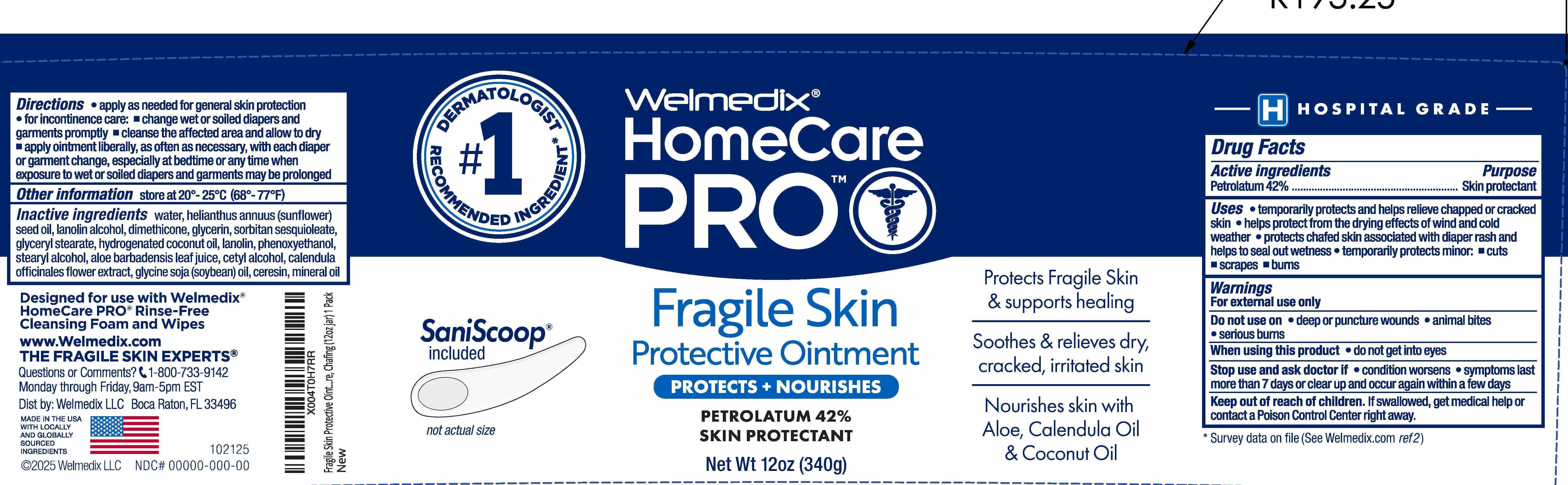 DRUG LABEL: Welmedix HomeCare PRO Fragile Skin Protectant
NDC: 24330-413 | Form: OINTMENT
Manufacturer: Welmedix LLC
Category: otc | Type: HUMAN OTC DRUG LABEL
Date: 20251113

ACTIVE INGREDIENTS: PETROLATUM 42 g/100 g
INACTIVE INGREDIENTS: WATER; HELIANTHUS ANNUUS (SUNFLOWER) SEED OIL; LANOLIN ALCOHOL; DIMETHICONE; GLYCERIN; SORBITAN SESQUIOLEATE; GLYCERYL MONOSTEARATE; HYDROGENATED COCONUT OIL; LANOLIN; PHENOXYETHANOL; STEARYL ALCOHOL; ALOE BARBADENSIS LEAF JUICE; CETYL ALCOHOL; CALENDULA OFFICINALIS FLOWER; CERESIN; MINERAL OIL; GLYCINE SOJA (SOYBEAN) OIL UNSAPONIFIABLES

Welmedix®HomeCare PRO Fragile Skin Protective Ointment

Active ingredients

Petrolatum 42%

Purpose

Skin Protectant

Uses

- temporarily protects and helps relieve chapped or cracked skin
- helps protect from the drying effects of wind and cold weather
- helps treat and prevent diaper rash
- protects chafed skin associated with diaper rash and helps protect from wetness
- temporarily protects: • minor cuts • scrapes • burns

Warnings

For external use only

Do not use on

- deep or puncture wounds
- animal bites
- serious burns

When using this product do not get into eyes

Stop use and ask a doctor if

- condition worsens
- symptoms last more than 7 days or clear up and occur again within a few days.

Keep out of reach of children

If swallowed, get medical help or consult a Poison Control Center right away.

Directions:

For general skin protection: apply as needed.

For incontinence care: change wet and soiled diapers and garments promptly. • Cleanse the affected area and allow to dry. • Apply ointment liberally, as often as necessary, especially at bedtime or any time when exposure to wet, moist or soiled garments may be prolonged.

Other Information:

Store at 20-25° C (68-77° F)

Inactive ingredients

water, helianthus annuus (sunflower) seed oil, lanolin alcohol, dimethicone, glycerin, sorbitan sesquioleate, glyceryl stearate, hydrogenated coconut oil, lanolin, phenoxyethanol, stearyl alcohol, aloe barbadensis leaf juice, cetyl alcohol, calendula officinales flower extract, glycine soja (soybean) oil, ceresin, mineral oil

Principal Display Panel

Welmedix®

HomeCare
PRO

Fragile Skin
Protective Ointment

PROTECTS + NOURISHES

PETROLATUM 42%

SKIN PROTECTANT

Net Wt 12 oz (340g)